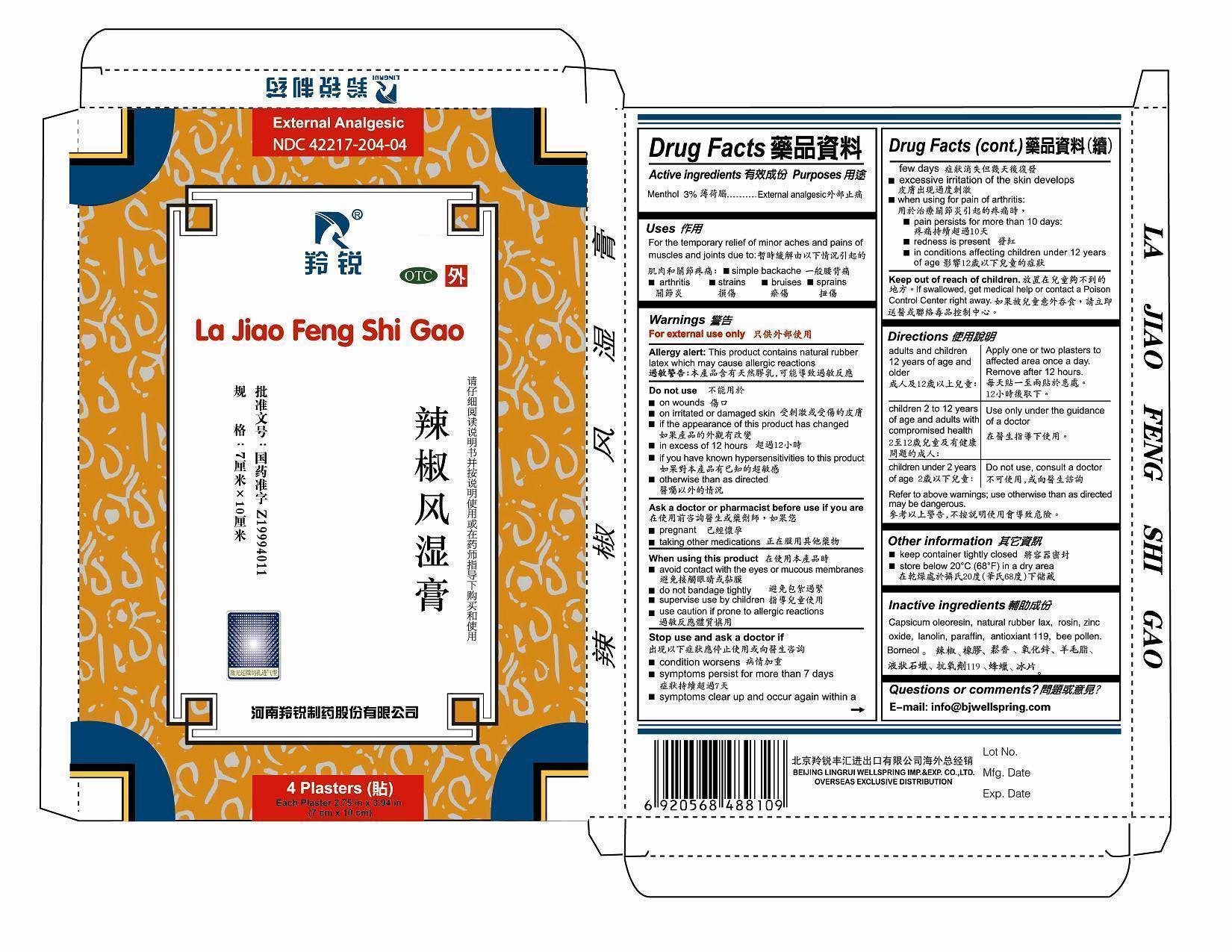 DRUG LABEL: La Jiao Feng Shi Gao
NDC: 42217-204 | Form: PLASTER
Manufacturer: Henan Lingrui Pharmaceutical Co Ltd
Category: otc | Type: HUMAN OTC DRUG LABEL
Date: 20141121

ACTIVE INGREDIENTS: MENTHOL 3.0 g/100 g
INACTIVE INGREDIENTS: CAPSICUM OLEORESIN; NATURAL LATEX RUBBER; ROSIN; ZINC OXIDE; LANOLIN; PARAFFIN; ANTIOXIDANT 119; BEE POLLEN; BORNEOL

Henan Lingrui Pharmaceutical Co Ltd

ACTIVE INGREDIENTS

Menthol 3%

PURPOSE

Menthol External Analgesic

USES

For the temporary relief of minor aches and pains of muscles and joints due to:

simple backache

arthritis

strains

bruises

sprains

Warnings

For External Use only.

Allergy Alert: This product contains natural rubber latex which may cause allergic reactions.

Do not use

on wounds

on irritated or damaged skin

if the appearance of this product has changed

in excess of 12 hours

if you have known hypersensitives to this product

otherwise than as directed

ASK A DOCTOR OR PHARMACIST BEFORE USE IF YOU ARE

pregnant

taking other medications

When using this product

avoid contact with the eye or mucous membrances

do not bandage tightly

supervise use by children

use caution if prone to allergic reactions

STOP USE AND ASK A DOCTOR IF

condition worsens

symptoms persist for more than 7 days

symptoms clear up and occur again within a few days

excessive irritaion of the skin develops

when using for pain of athritis

pain persists for more than 10 days

redness is present

in conditions affecting children under 12 years of age

Keep out of reach of children.

If swallowed, get medical help or contact a Poison Control Center right away.

DIRECTIONS

Adults and children 12 years of age and older: Apply one or two plasters to affected area once a day. Remove after 12 hours.
Children 2 to 12 years of age and adults with compromised health: Use only under the guidance of a doctor.
Children under 2 years of age: Do not use, consult a doctor.
Refer to the above warnings: use otherwise than as directed may be dangerous.

Other Information

Keep container tightly closed.

Store below 20 degree centigrade (68 E F) in a dry area.

Inactive Ingredients

CAPSICUM OLEORESIN, NATURAL LATEX RUBBER, ROSIN. ZINC OXIDE, COCONUT OIL, LANOLIN, PARAFFIN, ANTIOXIDANT 119, BEE POLLEN, BORNEOL

Questions or Comments?

E-mail: info@bjwellspring.com